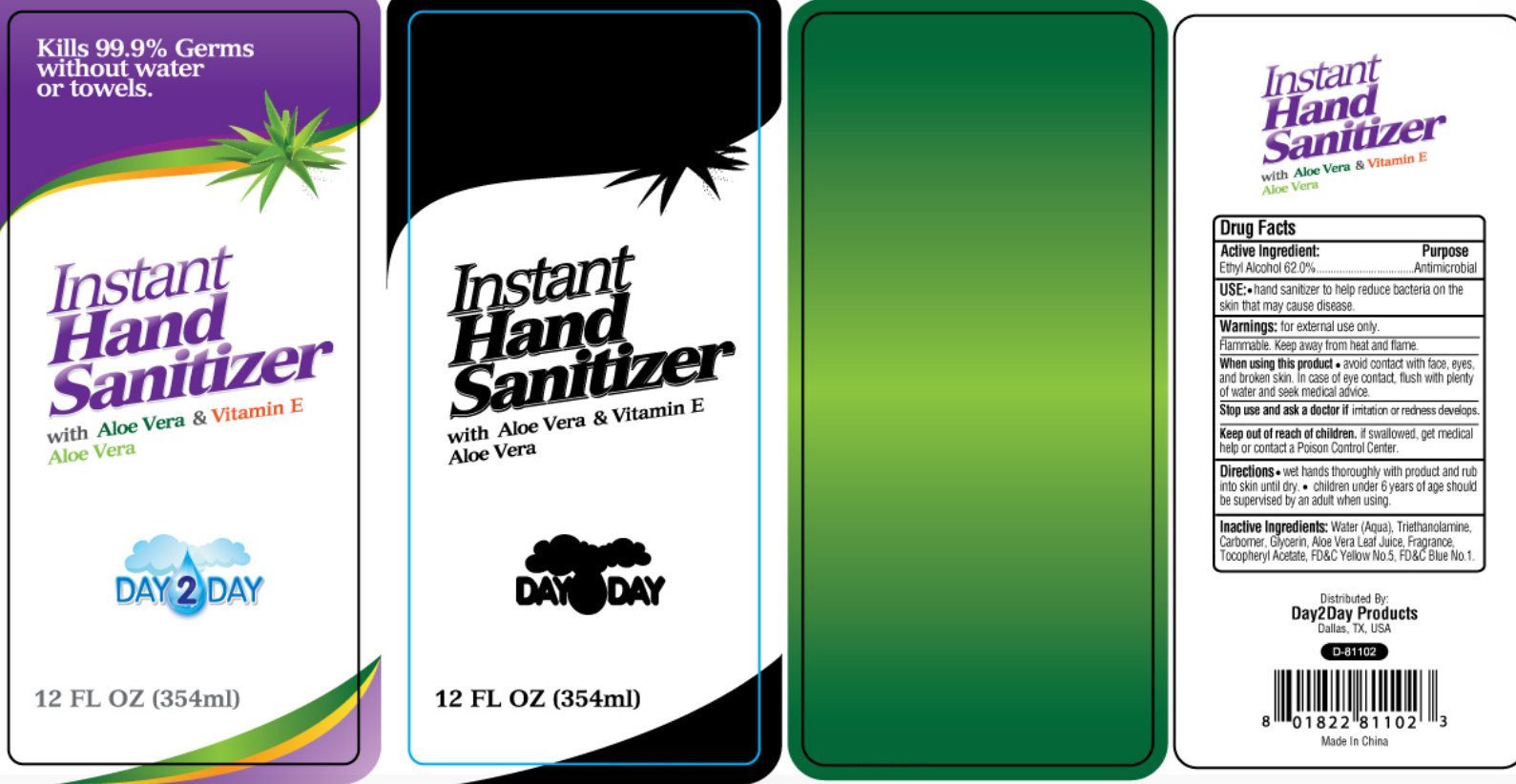 DRUG LABEL: Instant Hand Sanitizer Original With Aloe Vera And Vitamin E
NDC: 76088-301 | Form: LIQUID
Manufacturer: King Import Warehouse
Category: otc | Type: HUMAN OTC DRUG LABEL
Date: 20110330

ACTIVE INGREDIENTS: ALCOHOL 62 mL/100 mL
INACTIVE INGREDIENTS: WATER; TROLAMINE; GLYCERIN; ALOE VERA LEAF; ALPHA-TOCOPHEROL ACETATE; FD&C YELLOW NO. 5; FD&C BLUE NO. 1

DAY2DAY Instant Hand Sanitizer With Aloe Vera & Vitamin E

Active Ingredient:

Ethyl Alcohol 62.0%

Purpose

Antimicrobial

INDICATIONS AND USAGE

USE: hand sanitizer to help reduce bacteria on the skin that may cause disease.

Warnings: for external use only.

STORAGE AND HANDLING

Flammable. Keep away from heat and flame.

When using this product

- avoid contact with face, eyes, and broken skin. In case of eye contact, flush with plenty of water and seek medical advice.

Stop use and ask a doctor if irritation or redness develops.

Keep out of reach of children. If swallowed, get medical help or contact a Poison Control Center.

Directions

- wet hands thoroughly with product and rub into skin until dry.
- children under 6 years of age should be supervised by an adult when using.

INACTIVE INGREDIENT

Inactive Ingredients:Water (Aqua), Triethanolamine, Carbomer, Aloe Vera Leaf Juice, Fragrance, Tocopheryl Acetate.

PACKAGE LABEL

Kills 99.9% Germs without water or towels.

Instant Hand Sanitizer

with Aloe Vera and Vitamin E

Day2Day

12 FL OZ (354ml)